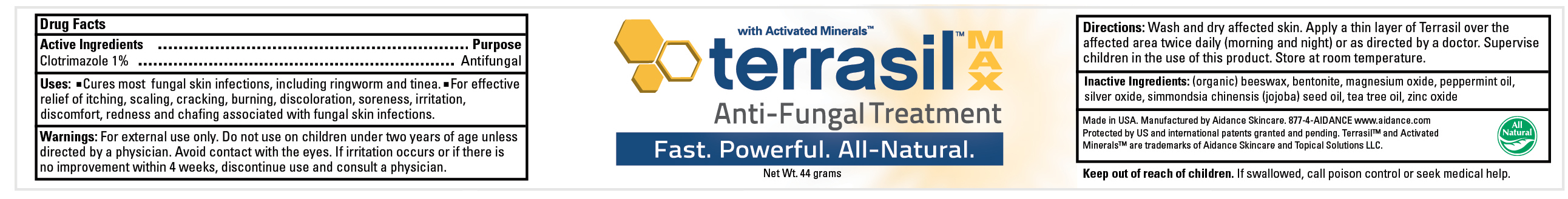 DRUG LABEL: TERRASIL ANTI-FUNGAL TREATMENT
								
NDC: 24909-107 | Form: OINTMENT
Manufacturer: Aidance Skincare & Topical Solutions, LLC
Category: otc | Type: HUMAN OTC DRUG LABEL
Date: 20120126

ACTIVE INGREDIENTS: CLOTRIMAZOLE 1.0 g/100 g
INACTIVE INGREDIENTS: BENTONITE; JOJOBA OIL; MAGNESIUM OXIDE; PEPPERMINT OIL; SILVER OXIDE; TEA TREE OIL; WHITE WAX; ZINC OXIDE

Drug Facts

Active Ingredient

Clotrimazole 1.0%

Purpose

Antifungal

Uses

- Cures most fungal skin infections, including ringworm and tinea.
- For effective relief of itching, scaling, cracking, burning, discoloration, soreness, irritation, discomfort, redness and chafing associated with fungal skin infections.

Warnings

For external use only. Do not use on children under two years of age unless directed by a physician. Avoid contact with the eyes. If irritation occurs or if there is no improvement within 4 weeks, discontinue use and consult a physician.

Keep out of reach of children.

If swallowed, call poison control or seek medical help.

Directions

Wash and dry affected skin. Apply a thin layer of Terrasil over the affected area twice daily (morning and night) or as directed by a doctor. Supervise children in the use of this product. Store at room temperature.

Inactive Ingredients

(Organic) Beeswax, Bentonite, Magnesium Oxide, Peppermint Oil, Silver Oxide, Simmondsia Chinensis (Jojoba) Seed Oil, Tea Tree Oil, Zinc Oxide

PACKAGE LABEL

Place holder text